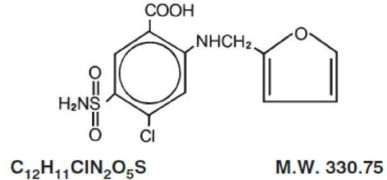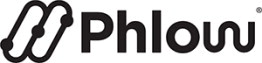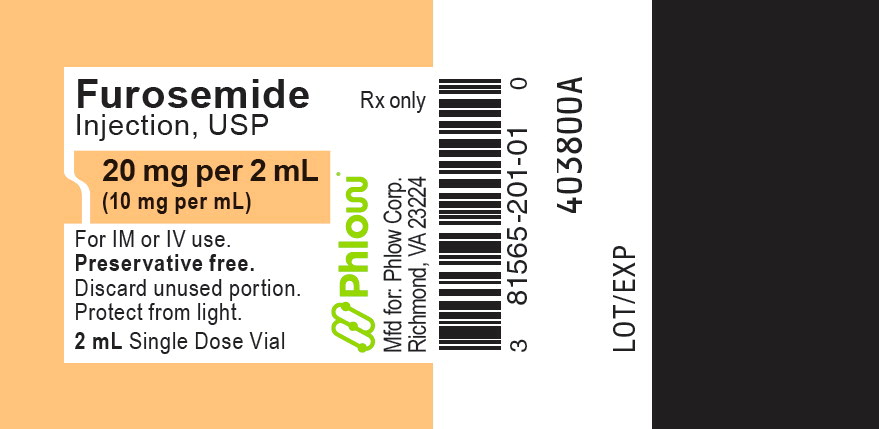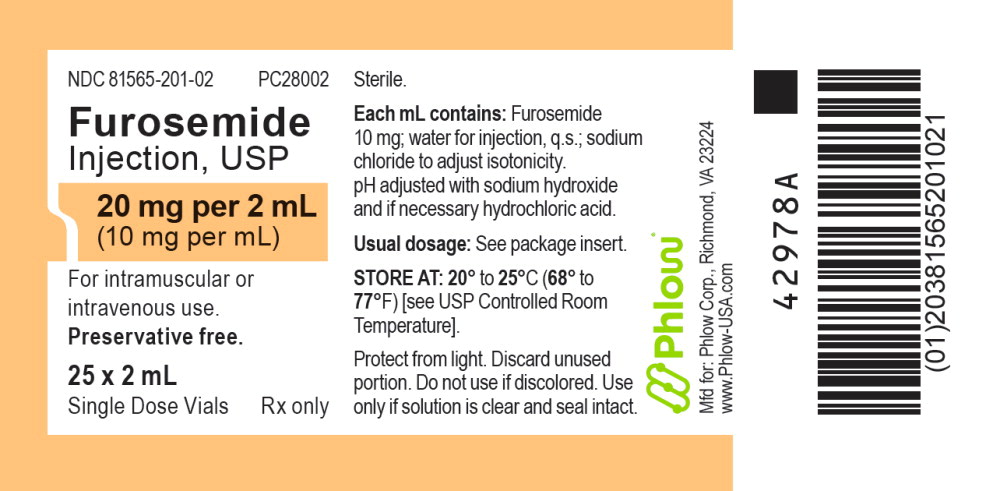 DRUG LABEL: Furosemide
NDC: 81565-201 | Form: INJECTION, SOLUTION
Manufacturer: Phlow Corporation
Category: prescription | Type: HUMAN PRESCRIPTION DRUG LABEL
Date: 20260109

ACTIVE INGREDIENTS: FUROSEMIDE 10 mg/1 mL
INACTIVE INGREDIENTS: SODIUM CHLORIDE; SODIUM HYDROXIDE; HYDROCHLORIC ACID; WATER

HIGHLIGHTS OF PRESCRIBING INFORMATION

These highlights do not include all the information needed to use FUROSEMIDE INJECTION safely and effectively. See full prescribing information for FUROSEMIDE INJECTION.
FUROSEMIDE INJECTION (furosemide), for intravenous or intramuscular use
Initial U.S. Approval: 1982

1 INDICATIONS AND USAGE

Furosemide Injection is a loop diuretic indicated for:

- The treatment of edema associated with heart failure, cirrhosis of the liver, and renal disease (1.1)
- Acute pulmonary edema as adjunctive therapy (1.2)

2 DOSAGE AND ADMINISTRATION

Edema:

- Initial dose is 20 mg to 40 mg once given intramuscularly or intravenously. The intravenous dose should be administered slowly over 1 minute to 2 minutes (2.2)
- If needed, a second dose may be administered 2 hours after the first dose (2.2)

Acute Pulmonary Edema:

- Initial dose is 40 mg injected slowly intravenously over 1 minute to 2 minutes (2.2)
- If needed, a second dose is 80 mg injected intravenously slowly in 1 minute to 2 minutes (2.2)

Pediatric Dosage:

- The initial dose in pediatric patients is 1 mg/kg body weight once given slowly intramuscularly or intravenously. If needed, dosage may be increased by 1 mg/kg not sooner than 2 hours after the previous dose, until the desired diuretic effect has been obtained. Doses greater than 6 mg/kg body weight are not recommended (2.3)

3 DOSAGE FORMS AND STRENGTHS

Injection: Furosemide Injection, USP is supplied as a sterile, colorless solution as

- 20 mg/2 mL (10 mg/mL) in a single-dose vial (3)

4 CONTRAINDICATIONS

- Anuria (4)
- Hypersensitivity to furosemide (4)

5 WARNINGS AND PRECAUTIONS

- Fluid, Electrolyte, and Metabolic Abnormalities: Monitor serum electrolytes, CO2, BUN, creatinine, glucose, and uric acid (5.1)
- Worsening Renal Function: Monitor for dehydration and azotemia. (5.2)
- Ototoxicity: Avoid rapid injection and higher than recommended doses. (5.3, 7.1)
- Acute Urinary Retention: Monitor patients with symptoms of urinary retention. (5.4)

6 ADVERSE REACTIONS

Most common adverse reactions are related to fluid and electrolyte imbalance (6)

To report SUSPECTED ADVERSE REACTIONS, contact Fresenius Kabi USA, LLC at 1-800-551-7176 or FDA at 1-800-FDA-1088 or www.fda.gov/medwatch.

7 DRUG INTERACTIONS

- Aminoglycoside antibiotics: Increased potential ototoxicity of the antibiotics. Avoid combination (7.1)
- Ethacrynic acid: Risk of ototoxicity. Avoid combination (7.1)
- Salicylates: Risk of salicylate toxicity (7.1)
- Cisplatin and nephrotoxic drugs: Risk of ototoxicity and nephrotoxicity (7.1)
- Lithium: Risk of lithium toxicity (7.1)
- Renin-angiotensin inhibitors: Increased risk of hypotension and renal failure. (7.1)
- Adrenergic blocking drugs: Risk of potentiation (7.1)
- Drugs undergoing renal tubular secretion: Risk of toxicity potentiation (7.1)

FULL PRESCRIBING INFORMATION

1 INDICATIONS AND USAGE

1.1 Edema

Furosemide Injection is indicated in adults and pediatric patients for the treatment of edema associated with heart failure, cirrhosis of the liver, and renal disease, including the nephrotic syndrome.

1.2 Acute Pulmonary Edema

Furosemide Injection is indicated as adjunctive therapy in acute pulmonary edema.

2 DOSAGE AND ADMINISTRATION

2.1 General Considerations

Inspect Furosemide Injection visually for particulate matter and discoloration before administration.

2.2 Recommended Dosage for Adults

Edema

Individualize therapy according to patient response.

The usual initial dose of furosemide is 20 mg to 40 mg given as a single-dose, injected intramuscularly or intravenously. Give the intravenous dose slowly (over 1 minute to 2 minutes). If needed, administer another dose in the same manner 2 hours later or increase the dose. The dose may be raised by 20 mg and administered not sooner than 2 hours after the previous dose until the desired diuretic effect has been obtained. Administer this individually determined single-dose once or twice daily.

If the physician elects to use high-dose parenteral therapy, add the furosemide to either 0.9% Sodium Chloride Injection USP, Lactated Ringer's Injection USP, or Dextrose Injection 5%, USP, after pH has been adjusted to above 5.5, and administer as a controlled intravenous infusion at a rate not greater than 4 mg/min. Furosemide Injection is a buffered alkaline solution with a pH of about 9 and the drug may precipitate at pH values below 7. Care must be taken to ensure that the pH of the prepared infusion solution is in the weakly alkaline to neutral range. Acid solutions, including other parenteral medications (e.g., labetalol, ciprofloxacin, amrinone, milrinone) must not be administered concurrently in the same infusion because they may cause precipitation of the furosemide.

Acute Pulmonary Edema

The usual initial dose of furosemide is 40 mg injected slowly intravenously (over 1 minute to 2 minutes). If a satisfactory response does not occur within 1 hour, increase the dose to 80 mg injected slowly intravenously (over 1 minute to 2 minutes).

2.3 Recommended Dosage for Pediatric Patients

The usual initial dose of Furosemide Injection (intravenously or intramuscularly) in pediatric patients is 1 mg/kg body weight administered slowly (over 1 minute to 2 minutes). If the diuretic response to the initial dose is not satisfactory, dosage may be increased by 1 mg/kg not sooner than 2 hours after the previous dose, until the desired diuretic effect has been obtained. Doses greater than 6 mg/kg body weight are not recommended.

The maximum dose for premature infants should not exceed 1 mg/kg/day [see Use in Specific Populations (8.4)].

3 DOSAGE FORMS AND STRENGTHS

Injection: Furosemide Injection, USP is supplied as a sterile, colorless solution as

- 20 mg/2 mL (10 mg/mL) in a single-dose vial

4 CONTRAINDICATIONS

- Furosemide Injection is contraindicated in patients with anuria.
- Furosemide Injection is contraindicated in patients with a history of hypersensitivity to furosemide.

5 WARNINGS AND PRECAUTIONS

5.1 Fluid, Electrolyte, and Metabolic Abnormalities

Furosemide may cause fluid, electrolyte, and metabolic abnormalities such as hypovolemia, hypokalemia, azotemia, hyponatremia, hypochloremic alkalosis, hypomagnesemia, hypocalcemia, hyperglycemia, or hyperuricemia, particularly in patients receiving higher doses, patients with inadequate oral electrolyte intake, and in elderly patients. Excessive diuresis may cause dehydration and blood volume reduction with circulatory collapse and possibly vascular thrombosis and embolism, particularly in elderly patients. Serum electrolytes, CO2, BUN, creatinine, glucose, and uric acid should be monitored frequently during furosemide therapy.

In patients with hepatic cirrhosis and ascites, sudden alterations of fluid and electrolyte balance may precipitate hepatic encephalopathy and coma. Treatment in such patients is best initiated in the hospital with small doses and careful monitoring of the patient's clinical status and electrolyte balance.

5.2 Worsening Renal Function

Furosemide can cause dehydration and azotemia. If increasing azotemia and oliguria occur during treatment of severe progressive renal disease, furosemide should be discontinued [see Clinical Pharmacology (12.3)].

Furosemide use in the first year of life, especially in patients born pre-term, may precipitate nephrocalcinosis/nephrolithiasis. Therefore renal function must be monitored and renal ultrasonography performed in this age group [see Use in Specific Populations (8.4)].

5.3 Ototoxicity

Cases of tinnitus and reversible or irreversible hearing impairment and deafness have been reported. Reports usually indicate that furosemide ototoxicity is associated with rapid injection, severe renal impairment, the use of higher than recommended doses, hypoproteinemia or concomitant therapy with aminoglycoside antibiotics, ethacrynic acid, or other ototoxic drugs. If the physician elects to use high-dose parenteral therapy, controlled intravenous infusion is advisable (for adults, an infusion rate not exceeding 4 mg furosemide per minute has been used) [see Drug Interactions (7.1)].

Hearing loss in neonates, including premature neonates has been associated with the use of Furosemide Injection [see Use in Specific Populations (8.4)].

5.4 Acute Urinary Retention

In patients with severe symptoms of urinary retention (because of bladder emptying disorders, prostatic hyperplasia, urethral narrowing), the administration of furosemide can cause acute urinary retention related to increased production and retention of urine. Thus, these patients require careful monitoring, especially during the initial stages of treatment.

6 ADVERSE REACTIONS

The following adverse reactions are described elsewhere in the labeling:

- Fluid, Electrolyte, and Metabolic Abnormalities [see Warnings and Precautions (5.1)]
- Ototoxicity [see Warnings and Precautions (5.3)]

The following adverse reactions associated with the use of furosemide were identified in clinical studies or postmarketing reports. Because some of these reactions were reported voluntarily from a population of uncertain size, it is not always possible to reliably estimate their frequency or establish a causal relationship to drug exposure.

Adverse reactions are categorized below by organ system and listed by decreasing severity.

Gastrointestinal System Reactions: pancreatitis, jaundice (intrahepatic cholestatic jaundice), increased liver enzymes, anorexia, oral and gastric irritation, cramping, diarrhea, constipation, nausea, vomiting.

Systemic Hypersensitivity Reactions: severe anaphylactic or anaphylactoid reactions (e.g., with shock), systemic vasculitis, interstitial nephritis, necrotizing angiitis.

Central Nervous System Reactions: tinnitus and hearing loss, paresthesias, vertigo, dizziness, headache, blurred vision, xanthopsia.

Hematologic Reactions: aplastic anemia, thrombocytopenia, agranulocytosis, hemolytic anemia, leukopenia, anemia, eosinophilia.

Dermatologic-Hypersensitivity Reactions: toxic epidermal necrolysis, Stevens-Johnson Syndrome, erythema multiforme, drug rash with eosinophilia and systemic symptoms, acute generalized exanthematous pustulosis, exfoliative dermatitis, bullous pemphigoid, purpura, photosensitivity, rash.

Cardiovascular Reactions: orthostatic hypotension, increase in cholesterol and triglyceride serum levels.

Other Reactions: glycosuria, muscle spasm, weakness, restlessness, urinary bladder spasm, thrombophlebitis, transient injection site pain following intramuscular injection, fever.

7 DRUG INTERACTIONS

7.1 Effects of Furosemide on Other Drugs

Drug/Substance Class or Name | Drug Interaction Effect | Recommendations
Aminoglycoside antibiotics | Furosemide may increase the ototoxic potential of aminoglycoside antibiotics, especially in the presence of impaired renal function [see Warnings and Precautions (5.3)]. | Avoid combination except in life-threatening situations.
Ethacrynic acid | Possibility of ototoxicity [see Warnings and Precautions (5.3)]. | Avoid concomitant use with ethacrynic acid.
Salicylates | May experience salicylate toxicity at lower doses because of competitive renal excretory sites. | Monitor for symptoms of salicylate toxicity.
Cisplatin | There is a risk of ototoxic effects if cisplatin and furosemide are given concomitantly [see Warnings and Precautions (5.3)].
Cisplatin and nephrotoxic drugs | Nephrotoxicity | Administer furosemide at lower doses and with positive fluid balance when used to achieve forced diuresis during cisplatin treatment. Monitor renal function.
Paralytic agents | Furosemide has a tendency to antagonize the skeletal muscle relaxing effect of tubocurarine and may potentiate the action of succinylcholine. | Monitor for skeletal muscle effect.
Lithium | Furosemide reduces lithium's renal clearance and add a high-risk of lithium toxicity. | Avoid concomitant use with lithium.
Angiotensin converting enzyme inhibitors or angiotensin II receptor blockers | May lead to severe hypotension and deterioration in renal function, including renal failure. | Monitor for changes in blood pressure and renal function and interrupt or reduce the dosage of furosemide, angiotensin converting enzyme inhibitors, or angiotensin receptor blockers if needed.
Antihypertensive drugs | Furosemide may add to or potentiate the therapeutic effect of other antihypertensive drugs. | Monitor for changes in blood pressure and adjust the dose of other antihypertensive drugs if needed.
Adrenergic blocking drugs or peripheral adrenergic blocking drugs | Potentiation occurs. | Monitor for changes in blood pressure and adjust the dose of adrenergic blocking drugs if needed.
Norepinephrine | Furosemide may decrease arterial responsiveness (vasoconstricting effect) to norepinephrine. | Monitor blood pressure (or mean arterial pressure).
Chloral hydrate | In isolated cases, intravenous administration of furosemide within 24 hours of taking chloral hydrate may lead to flushing, sweating attacks, restlessness, nausea, increase in blood pressure, and tachycardia. | Concomitant use with chloral hydrate is not recommended.
Methotrexate and other drugs undergoing renal tubular secretion | Furosemide may decrease renal elimination of other drugs that undergo tubular secretion. High-dose treatment of furosemide may result in elevated serum levels of these drugs and may potentiate their toxicity. | Monitor serum levels of drugs undergoing renal tubular secretion and adjust the dose if needed.
Cephalosporin | Furosemide can increase the risk of cephalosporin-induced nephrotoxicity even in the setting of minor or transient renal impairment. | Monitor for changes in renal function.
Cyclosporine | Increased risk of gouty arthritis secondary to furosemide-induced hyperuricemia and cyclosporine impairment of renal urate excretion. | Monitor serum urate levels.
Thyroid hormones | High-doses (> 80 mg) of furosemide may inhibit the binding of thyroid hormones to carrier proteins and result in transient increase in free thyroid hormones, followed by an overall decrease in total thyroid hormone levels. | Monitor the total thyroid hormone levels.

7.2 Effects of Other Drugs on Furosemide

Drug/Substance Class or Name | Drug Interaction Effect | Recommendations
Phenytoin | Interferes directly with renal action of furosemide. | Monitor diuretic effects of furosemide and adjust the dose of furosemide if needed.
Methotrexate and other drugs undergoing renal tubular secretion | May reduce the effect of furosemide. High-dose treatment of methotrexate and these other drugs may result in elevated serum levels of furosemide and may potentiate the toxicity of furosemide. | Monitor for enhanced toxicity of furosemide.
Indomethacin | Coadministration of indomethacin may reduce the natriuretic and antihypertensive effects of furosemide in some patients by inhibiting prostaglandin synthesis. Indomethacin may also affect plasma renin levels, aldosterone excretion, and renin profile evaluation. | Patients receiving both indomethacin and furosemide should be observed closely to determine if the desired diuretic and/or antihypertensive effect of furosemide is achieved.

8 USE IN SPECIFIC POPULATIONS

8.1 Pregnancy

Risk Summary

Available data from published observational studies, case reports, and postmarketing reports, from decades of use, have not demonstrated a drug-associated risk of major birth defects, miscarriage, or other adverse maternal or fetal outcomes with furosemide use during pregnancy. Untreated congestive heart failure and cirrhosis of the liver can lead to adverse outcomes for the mother and the fetus (see Clinical Considerations).

In animal reproduction studies, furosemide has been shown to cause unexplained maternal deaths and abortions in rabbits when administered orally during organogenesis at 4 times a human i.v. dose of 80 mg based on body surface area (BSA) and oral bioavailability corrections, presumably secondary to volume depletion (see Data).

The estimated background risk for major birth defects and miscarriage for the indicated populations is unknown. All pregnancies have a background risk of birth defect, loss, or other adverse outcomes. In the U.S. general population, the estimated background risk of major birth defects and miscarriage in the clinically recognized pregnancies is 2 to 4% and 15 to 20%, respectively.

Clinical Considerations

Disease-Associated Maternal and/or Embryo/Fetal Risk

Pregnant women with congestive heart failure are at increased risk for pre-term birth. Stroke volume and heart rate increase during pregnancy, increasing cardiac output, especially during the first trimester. Clinical classification of heart disease may worsen with pregnancy and lead to maternal death and/or stillbirth. Closely monitor pregnant patients for destabilization of their heart failure.

Pregnant women with symptomatic cirrhosis generally have poor outcomes including hepatic failure, variceal hemorrhage, pre-term delivery, fetal growth restriction and maternal death. Outcomes are worse with coexisting esophageal varices. Pregnant women with cirrhosis of the liver should be carefully monitored and managed accordingly.

Data

Animal Data

The effects of furosemide on embryonic and fetal development and on pregnant dams were studied in mice, rats and rabbits.

Furosemide caused unexplained maternal deaths and abortions in the rabbit at the lowest dose of 25 mg/kg (approximately 4 times a human i.v. dose of 80 mg based on BSA and oral bioavailability corrections). In another study, a dose of 50 mg/kg (approximately 7 times a human i.v. dose of 80 mg based on BSA and oral bioavailability corrections) also caused maternal deaths and abortions when administered to rabbits between Days 12 and 17 of gestation. In a third study, none of the pregnant rabbits survived an oral dose of 100 mg/kg. Data from the above studies indicate fetal lethality that can precede maternal deaths.

The results of the mouse study and one of the three rabbit studies also showed an increased incidence and severity of hydronephrosis (distention of the renal pelvis and, in some cases, of the ureters) in fetuses of treated dams as compared with the incidence of fetuses from the control group.

8.2 Lactation

Risk Summary

The presence of furosemide has been reported in human milk. There are no data on the effects on the breastfed infant or the effects on milk production. Doses of furosemide associated with clinically significant diuresis may impair milk production. The developmental and health benefits of breastfeeding should be considered along with the mother's clinical need for furosemide and any potential adverse effects on the breastfed infant from furosemide or from the underlying maternal condition.

8.4 Pediatric Use

Published reports indicate that premature infants with post conceptual age (gestational plus postnatal) less than 31 weeks receiving doses exceeding 1 mg/kg/24 hours may develop plasma levels which could be associated with potential toxic effects including ototoxicity [see Warnings and Precautions (5.3)].

Furosemide in the first year of life, especially in patients born pre-term, may precipitate nephrocalcinosis/nephrolithiasis [see Warnings and Precautions (5.2)].

8.5 Geriatric Use

Controlled clinical studies of furosemide did not include sufficient numbers of subjects aged 65 and over to determine whether they respond differently from younger subjects. Other reported clinical experience has not identified differences in responses between the elderly and younger patients. In general, dose selection for the elderly patient should be cautious, usually starting at the low end of the dosing range, reflecting the greater frequency of decreased hepatic, renal or cardiac function, and of concomitant disease or other drug therapy.

This drug is known to be substantially excreted by the kidney, and the risk of toxic reactions to this drug may be greater in patients with impaired renal function. Because elderly patients are more likely to have decreased renal function, care should be taken in dose selection and it may be useful to monitor renal function [see Clinical Pharmacology (12.3)].

10 OVERDOSAGE

The principal signs and symptoms of overdose with furosemide are dehydration, blood volume reduction, hypotension, electrolyte imbalance, hypokalemia and hypochloremic alkalosis, and are extensions of its diuretic action.

The concentration of furosemide in biological fluids associated with toxicity or death is not known.

Treatment of overdosage is supportive and consists of replacement of excessive fluid and electrolyte losses. Serum electrolytes, carbon dioxide level, and blood pressure should be determined frequently. Adequate drainage must be assured in patients with urinary bladder outlet obstruction (such as prostatic hypertrophy).

Hemodialysis does not accelerate furosemide elimination.

11 DESCRIPTION

Furosemide is a diuretic which is an anthranilic acid derivative.

Chemically, it is 4-chloro-N-furfuryl-5- sulfamoylanthranilic acid.

Furosemide is a white to slightly yellow, odorless, crystalline powder. Practically insoluble in water; freely soluble in acetone, in dimethylformamide, and in solutions of alkali hydroxides; soluble in methanol; sparingly soluble in alcohol; slightly soluble in ether; very slightly soluble in chloroform. The structural formula is as follows:

Furosemide Injection, USP is a sterile, nonpyrogenic solution of furosemide in Water for Injection prepared with the aid of sodium hydroxide for intramuscular (IM) or intravenous (IV) use. Each mL contains: Furosemide 10 mg; sodium hydroxide 1.6 mg; Water for Injection q.s.; sodium chloride to adjust isotonicity; hydrochloric acid (q.s.) and/or sodium hydroxide (q.s.) to adjust pH between 8.0 and 9.3 if necessary.

12 CLINICAL PHARMACOLOGY

12.1 Mechanism of Action

Furosemide inhibits primarily the reabsorption of sodium and chloride not only in the proximal and distal tubules but also in the loop of Henle. The high degree of efficacy is largely due to this unique site of action. The action on the distal tubule is independent of any inhibitory effect on carbonic anhydrase and aldosterone.

12.2 Pharmacodynamics

The onset of diuresis following intravenous administration is within 5 minutes and somewhat later after intramuscular administration. The peak effect occurs within the first half hour. The duration of diuretic effect is approximately 2 hours.

12.3 Pharmacokinetics

Distribution

Furosemide is extensively bound to plasma proteins, mainly to albumin.

Plasma concentrations ranging from 1 to 400 mcg/mL are 91 to 99% bound in healthy individuals. The unbound fraction averages 2.3 to 4.1% at therapeutic concentrations.

Elimination

The terminal half-life of furosemide is approximately 2 hours.

Metabolism

Recent evidence suggests that furosemide glucuronide is the only or at least the major biotransformation product of furosemide in man.

Excretion

Significantly more furosemide is excreted in urine following the intravenous injection than after the tablet or oral solution.

Specific Populations

Geriatric Patients

Furosemide binding to albumin may be reduced in elderly patients. Furosemide is predominantly excreted unchanged in the urine. The renal clearance of furosemide after intravenous administration in older healthy male subjects (60 to 70 years of age) is statistically significantly smaller than in younger healthy male subjects (20 to 35 years of age). The initial diuretic effect of furosemide in older subjects is decreased relative to younger subjects [see Use in Specific Populations (8.5)].

Patients with Renal Impairment

One study in six subjects demonstrated that the combination of furosemide and acetylsalicylic acid temporarily reduced creatinine clearance in patients with chronic renal insufficiency. There are case reports of patients who developed increased BUN, serum creatinine and serum potassium levels, and weight gain when furosemide was used in conjunction with NSAIDs.

13 NONCLINICAL TOXICOLOGY

13.1 Carcinogenesis, Mutagenesis, Impairment of Fertility

Carcinogenesis

Furosemide was tested for carcinogenicity by oral administration in one strain of mice and one strain of rats. A small but significantly increased incidence of mammary gland carcinomas occurred in female mice at a dose approximately 8 times a human i.v. dose of 80 mg based on BSA and oral bioavailability corrections. There were marginal increases in uncommon tumors in male rats at a dose of 15 mg/kg but not at 30 mg/kg.

Mutagenesis

Furosemide was devoid of mutagenic activity in various strains of Salmonella typhimurium when tested in the presence or absence of an in vitro metabolic activation system, and questionably positive for gene mutation in mouse lymphoma cells in the presence of rat liver S9 at the highest dose tested. Furosemide did not induce sister chromatid exchange in human cells in vitro, but other studies on chromosomal aberrations in human cells in vitro gave conflicting results. In Chinese hamster cells it induced chromosomal damage but was questionably positive for sister chromatid exchange. Studies on the induction by furosemide of chromosomal aberrations in mice were inconclusive. The urine of rats treated with this drug did not induce gene conversion in Saccharomyces cerevisiae.

Impairment of Fertility

Furosemide produced no impairment of fertility in male or female rats, at 100 mg/kg/day (the maximum effective diuretic dose in the rat), approximately 7 times a human i.v. dose of 80 mg based on BSA and oral bioavailability corrections.

16 HOW SUPPLIED/STORAGE AND HANDLING

Store at room temperature 20°C to 25°C (68°F to 77°F); excursions permitted between 15°C and 30°C (59°F and 86°F). [See USP Controlled Room Temperature.] Protect from light.

Furosemide Injection, USP is a sterile, colorless solution for injection, available as a single-dose vial that contains 10 mg/mL of furosemide, and is supplied as follows:

Product Code | PC28002
Unit of Sale | NDC 81565-201-02 Unit of 25
Strength | 20 mg per 2 mL (10 mg per mL)
Each | NDC 81565-201-01 2 mL in a 2 mL single dose amber vial

Preservative Free.

Discard unused portion. Do not use if solution is discolored or contains particulate.

17 PATIENT COUNSELING INFORMATION

Fluid, Electrolyte, and Metabolic Abnormalities

Advise patients that they may experience symptoms from excessive fluid and/or electrolyte losses. The postural hypotension that sometimes occurs can usually be managed by getting up slowly. Potassium supplements and/or dietary measures may be needed to control or avoid hypokalemia [see Warnings and Precautions (5.1)].

Advise patients that furosemide may increase blood glucose levels and thereby affect urine glucose tests [see Warnings and Precautions (5.1)].

Photosensitivity

The skin of some patients may be more sensitive to the effects of sunlight while taking furosemide [see Adverse Reactions (6)].

Advise hypertensive patients to avoid medications that may increase blood pressure, including over-the-counter products for appetite suppression and cold symptoms [see Drug Interactions (7.1)].

For more information concerning this drug, please call Fresenius Kabi USA, LLC at 1-800-551-7176.

To report SUSPECTED ADVERSE REACTIONS, contact Fresenius Kabi USA, LLC at 1-800-551-7176 or FDA at 1-800-FDA-1088 or www.fda.gov/medwatch.

Mfd. for:

Richmond, VA 23224
www.Phlow-USA.com

Mfd. by:
Fresenius Kabi
Lake Zurich, IL 60047

451725A

PACKAGE LABEL

PACKAGE LABEL - PRINCIPAL DISPLAY - Furosemide 2 mL Single Dose Vial Label

Furosemide Injection, USP

20 mg per 2 mL (10 mg per mL)

For IM or IV use.
Preservative free.

Discard unused portion.
Protect from light.

2 mL Single Dose Vial

PACKAGE LABEL

PACKAGE LABEL - PRINCIPAL DISPLAY - Furosemide 2 mL Single Dose Vial Tray Label

NDC 81565-201-02 PC28002

Furosemide Injection, USP

20 mg per 2 mL (10 mg per mL)

For intramuscular or intravenous use.
Preservative free.

25 x 2 mL
Single Dose Vials Rx only